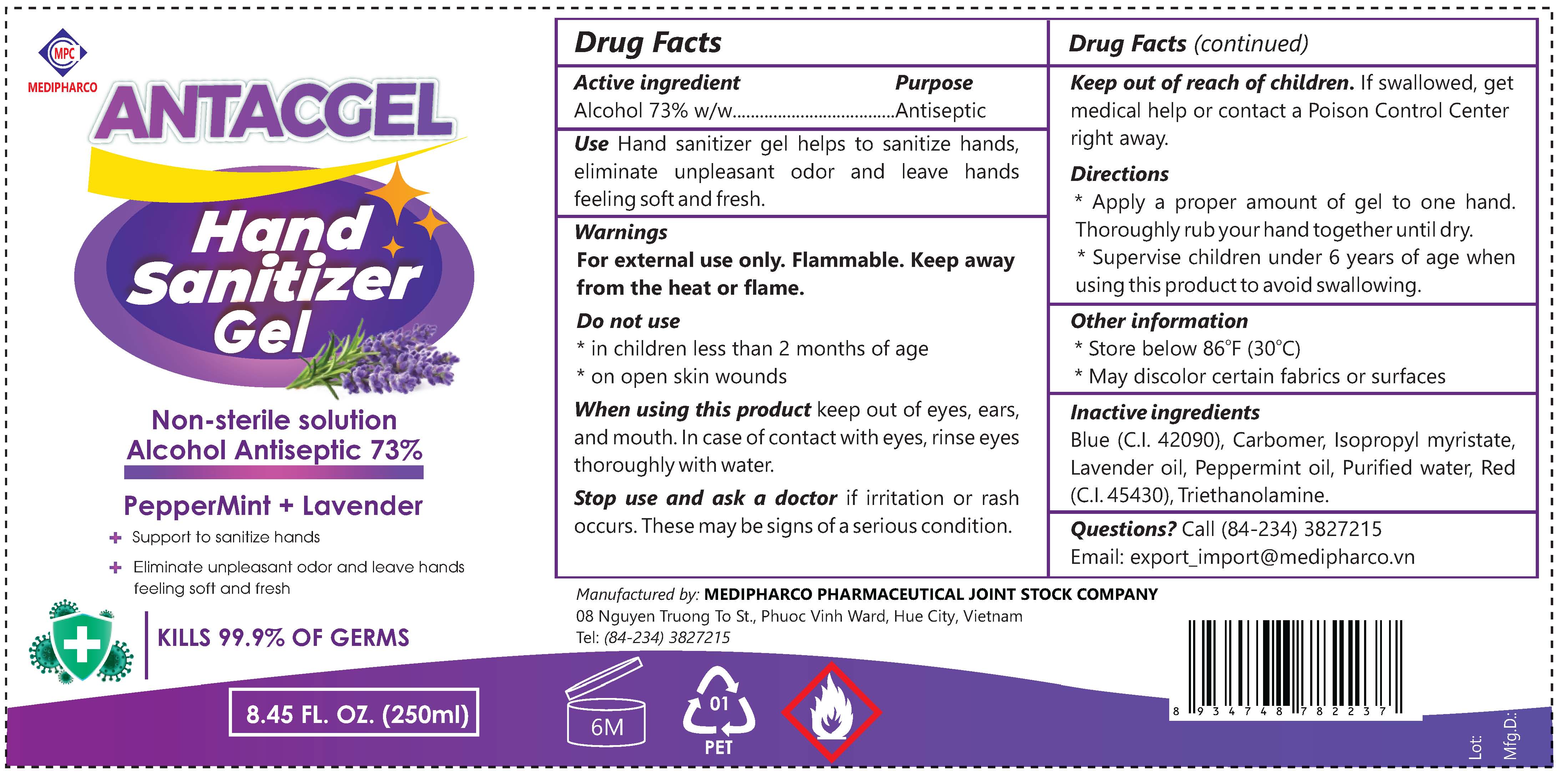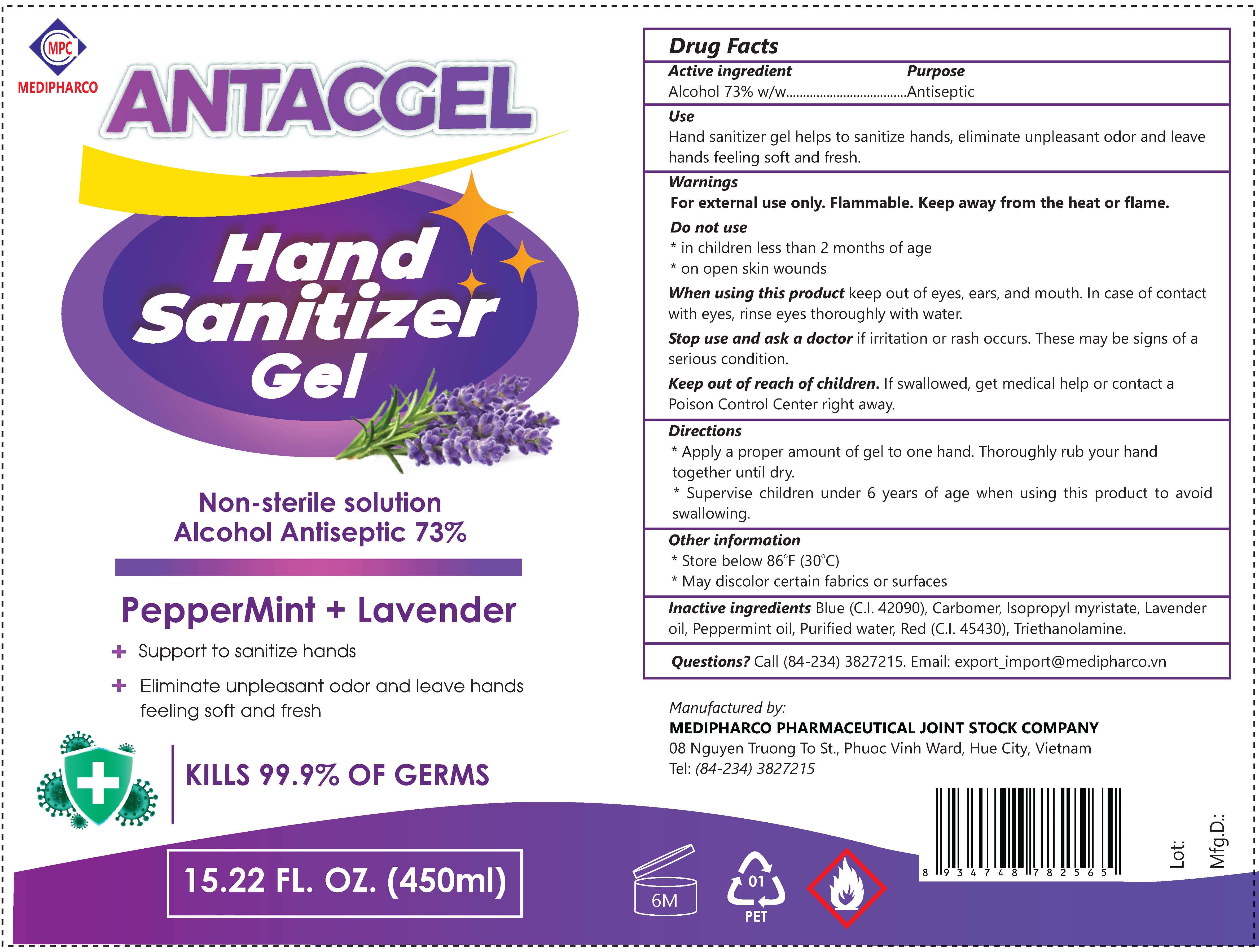 DRUG LABEL: ANTACGEL
NDC: 79633-202 | Form: GEL
Manufacturer: MEDIPHARCO PHARMACEUTICAL JOINT STOCK COMPANY
Category: otc | Type: HUMAN OTC DRUG LABEL
Date: 20200722

ACTIVE INGREDIENTS: ALCOHOL 73 g/100 g
INACTIVE INGREDIENTS: LAVENDER OIL; TROLAMINE; ERYTHROSINE SODIUM ANHYDROUS; WATER; ISOPROPYL MYRISTATE; CARBOMER 940; PEPPERMINT OIL; FD&C BLUE NO. 1

ACTIVE INGREDIENT

Alcohol 73%

PURPOSE

Antiseptic

INDICATIONS AND USAGE

Hand sanitizer gel helps to sanitize hands, eliminate unpleasant odor and leave hands feeling soft and fresh.

WARNINGS

For external use only. Flammable. Keep away from the heat or flame.

DO NOT USE

* in children less than 2 months of age
* on open skin wounds

WHEN USING

keep out of eyes, ears, and mouth. In case of contact with eyes, rinse eyes thoroughly with water.

STOP USE

if irritation or rash occurs. These may be signs of a serious condition.

KEEP OUT OF REACH OF CHILDREN

If swallowed, get medical help or contact a Poison Control Center right away.

STORAGE AND HANDLING

* Apply a proper amount of gel to one hand. Thoroughly rub your hand together until dry.
* Supervise children under 6 years of age when using this product to avoid swallowing.
* Store below 86ºF (30ºC)
* May discolor certain fabrics or surfaces

INACTIVE INGREDIENT

Blue (C.I. 42090), Carbomer, Isopropyl myristate, Lavender oil, Peppermint oil, Purified water, Red (C.I. 45430), Triethanolamine.

DOSAGE AND ADMINISTRATION

Apply a proper amount of gel to one hand.